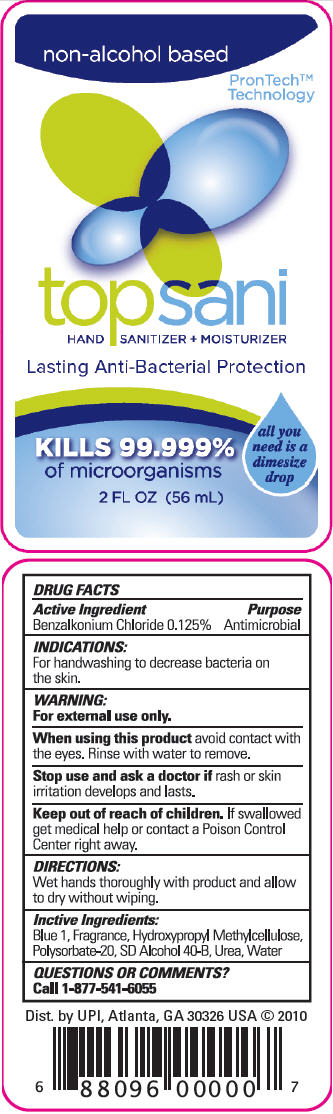 DRUG LABEL: TopSani
NDC: 24439-321 | Form: LIQUID
Manufacturer: United Promotions Inc.
Category: otc | Type: HUMAN OTC DRUG LABEL
Date: 20111201

ACTIVE INGREDIENTS: BENZALKONIUM CHLORIDE 1.25 mL/1000 mL
INACTIVE INGREDIENTS: ALCOHOL; FD&C BLUE NO. 1; HYPROMELLOSES; POLYSORBATE 20; UREA; WATER

topsani
HAND SANITIZER + MOISTURIZER

Drug Facts

Active Ingredients

Benzalkonium Chloride 0.125%

Purpose

Antimicrobial

Indications

For handwashing to decrease bacteria on the skin.

Warning

For external use only.

When using this product avoid contact with the eyes. Rinse with water to remove.

Stop use and ask a doctor if rash or irritation develops and lasts.

Keep out of reach of children. If swallowed get medical help or contact a poison control center right away.

Directions

Wet hands thoroughly with product and allow to dry without wiping.

Inactive Ingredients

Blue 1, Fragrance, Hydroxypropyl Methylcellulose, Polysorbate-20, SD Alcohol 40-B, Urea, Water

Questions or Comments?

Call 1-877-541-6055

Dist. by UPI, Atlanta, GA 30326 USA

PRINCIPAL DISPLAY PANEL - 56 mL Bottle Label

non-alcohol based

PronTech™
Technology

topsani
HAND SANITIZER + MOISTURIZER

Lasting Anti-Bacterial Protection

KILLS 99.999%
of microorganisms

all you
need is a
dimesize
drop

2 FL OZ (56 mL)